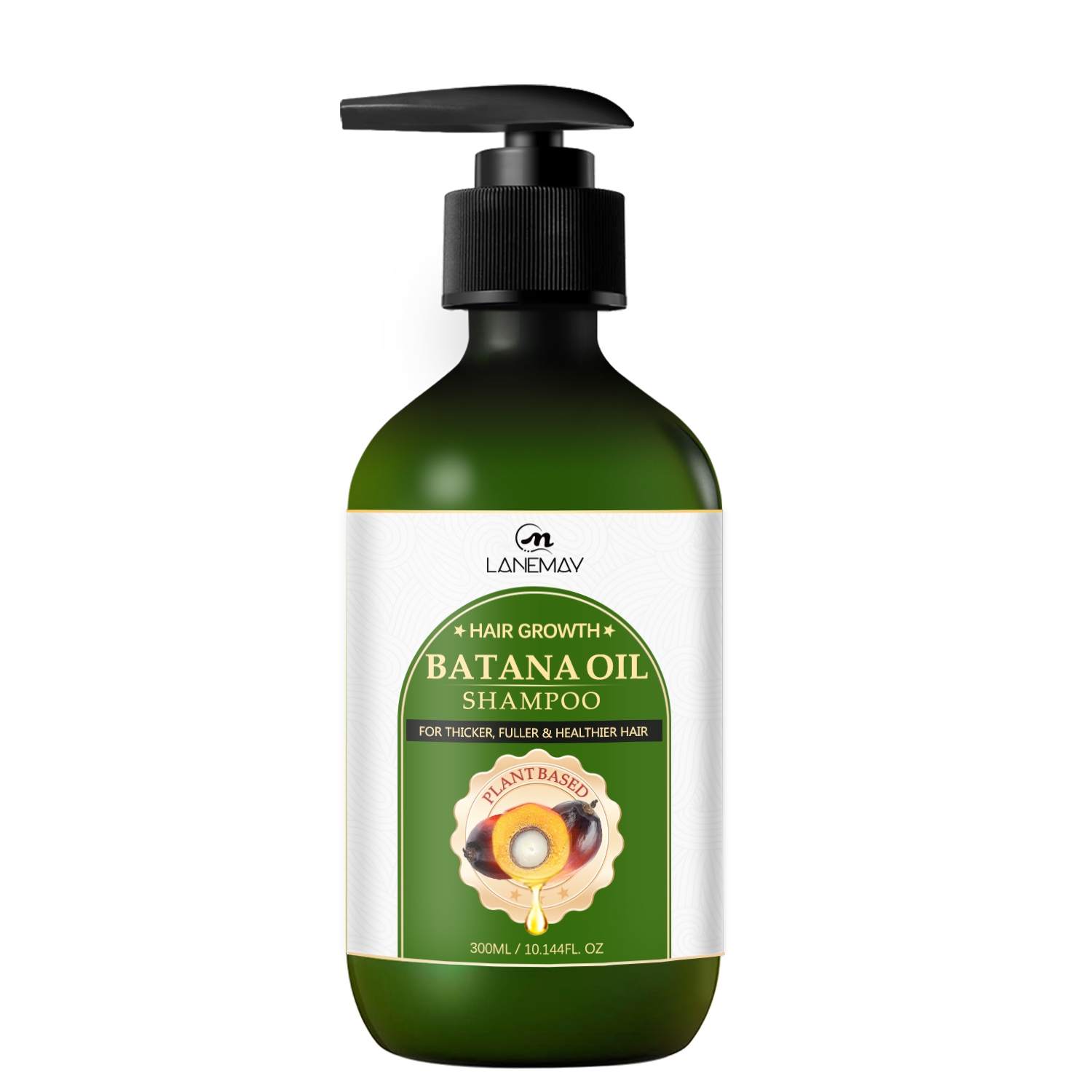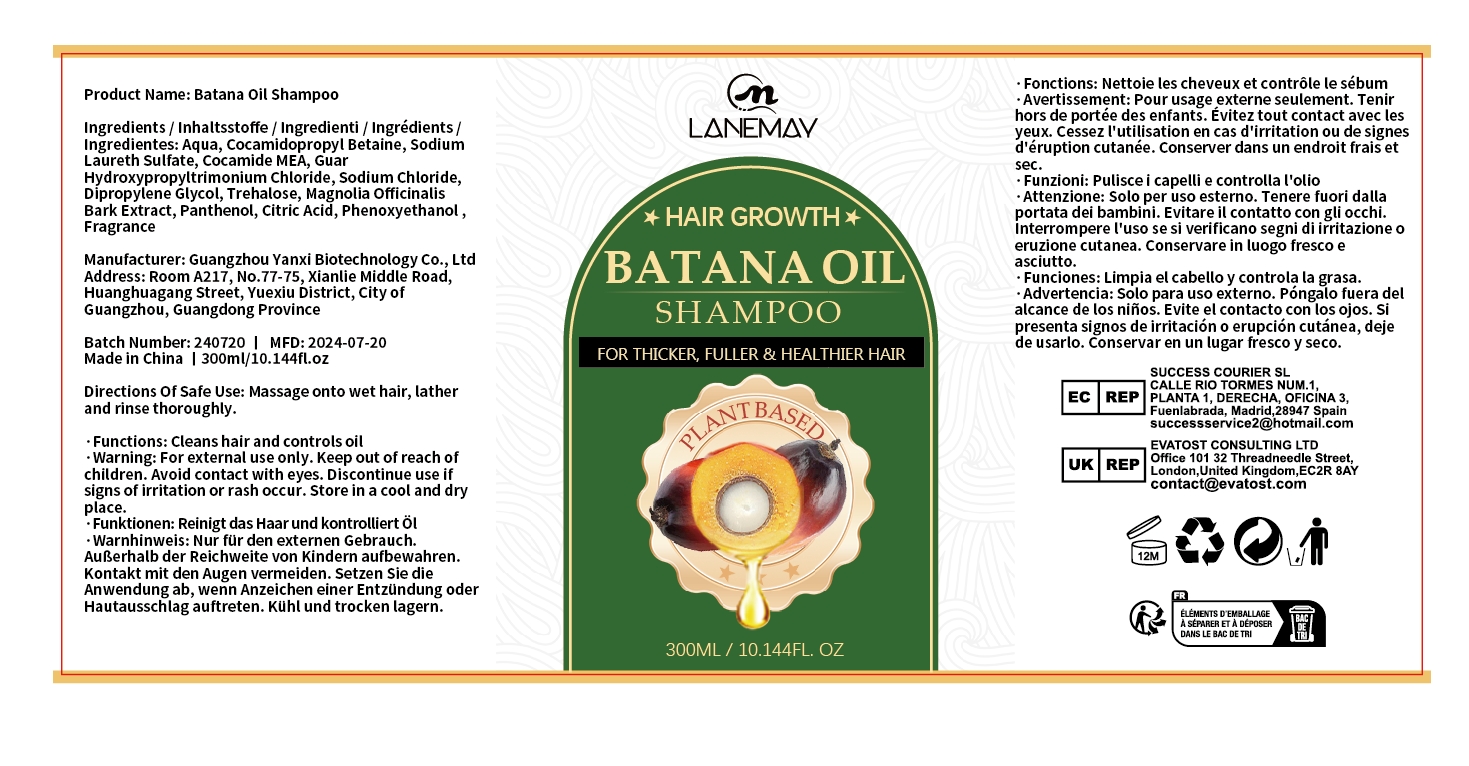 DRUG LABEL: Batana OilShampoo
NDC: 84025-190 | Form: SHAMPOO
Manufacturer: Guangzhou Yanxi Biotechnology Co.. Ltd
Category: otc | Type: HUMAN OTC DRUG LABEL
Date: 20240920

ACTIVE INGREDIENTS: DIPROPYLENE GLYCOL 3 mg/300 mL; COCAMIDOPROPYL BETAINE 5 mg/300 mL
INACTIVE INGREDIENTS: WATER

DOSAGE AND ADMINISTRATION

Shampoo for nourishing the scalp and smoothing the hair

INDICATIONS AND USAGE

Massage onto wet hair, latherand rinse thoroughly.

INACTIVE INGREDIENT

AQUA

WARNINGS

keep out of children

keep out of children

PURPOSE

Effectively keeps the hair smooth and reduces hair loss